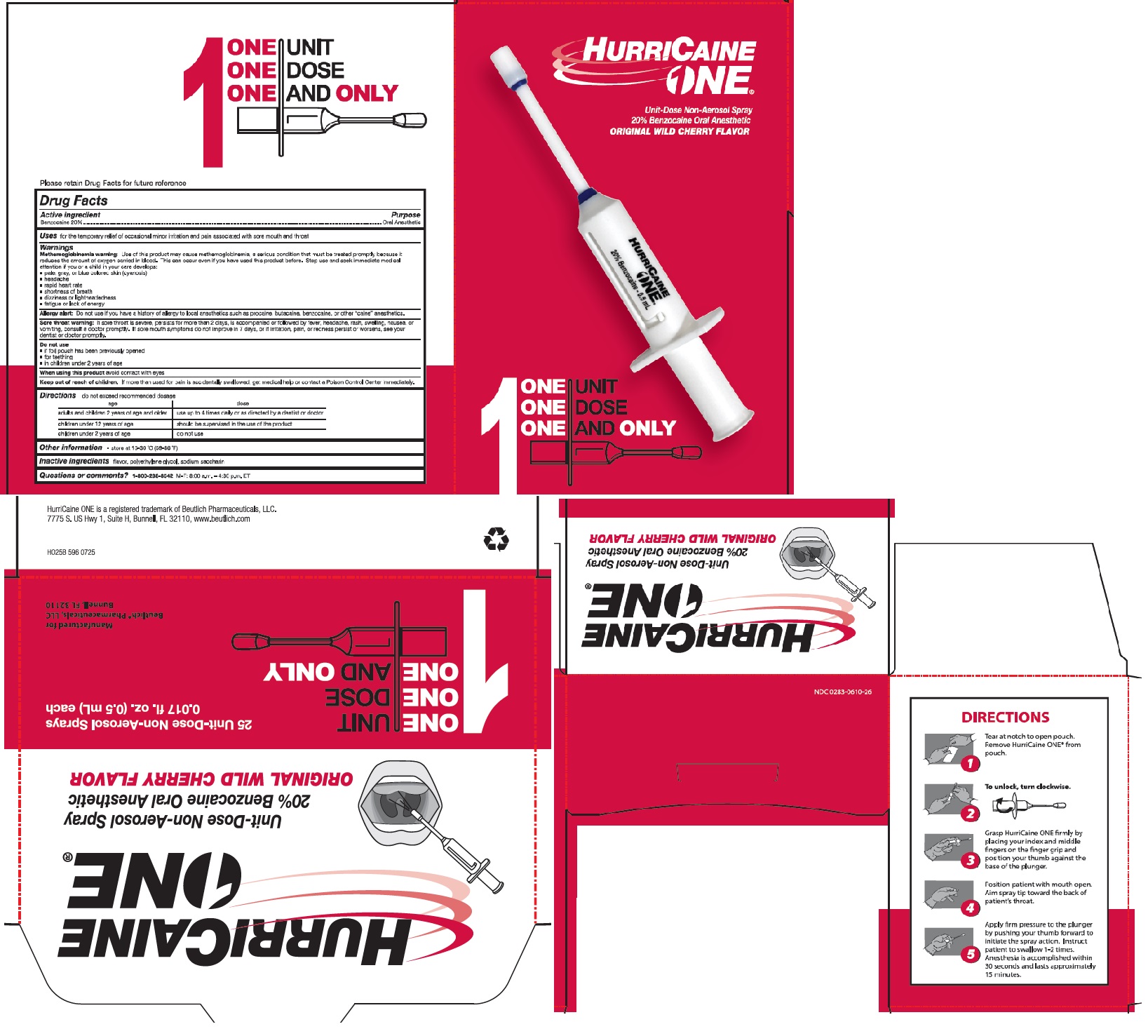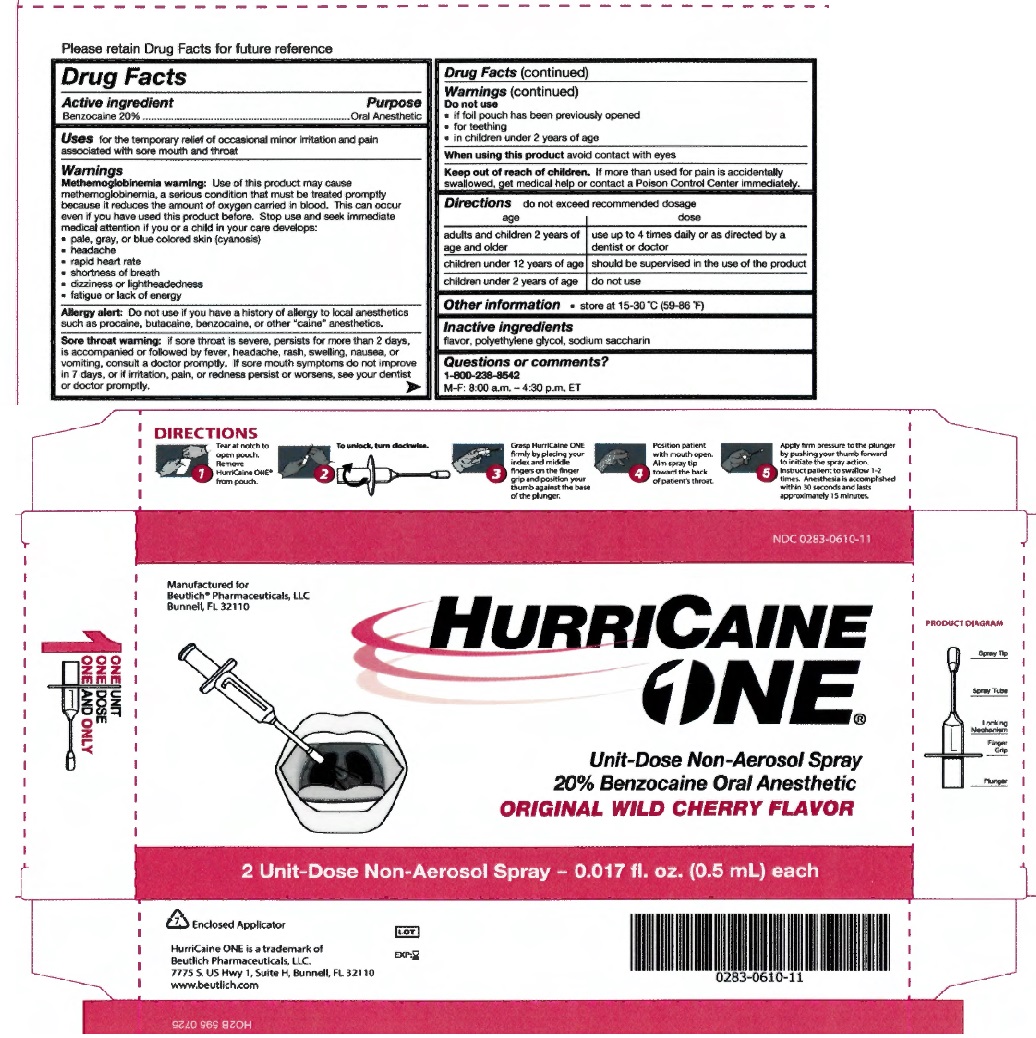 DRUG LABEL: HurriCaine
NDC: 0283-0610 | Form: SPRAY
Manufacturer: Beutlich Pharmaceuticals LLC
Category: otc | Type: HUMAN OTC DRUG LABEL
Date: 20251217

ACTIVE INGREDIENTS: BENZOCAINE 200 mg/1 g
INACTIVE INGREDIENTS: POLYETHYLENE GLYCOL 400 349 mg/1 g; SACCHARIN SODIUM 12 mg/1 g; CHERRY 439 mg/1 g

HurriCaine One
Drug Facts

Active Ingredient

Benzocaine 20%

Purpose

Oral Anesthetic

Uses

Uses for the temporary relief of occasional minor irritation and pain associated with sore mouth and throat

Warnings

Methemoglobinemia warning: Use of this product may cause methemoglobinemia, a serious condition that must be treated promptly because it reduces the amount of oxygen carried in blood. This can occur even if you have used this product before. Stop use and seek immediate medical attention if you or a child in your care develops:
• pale, gray, or blue colored skin (cyanosis)
• headache
• rapid heart rate
• shortness of breath
• dizziness or lightheadedness
• fatigue or lack of energy

Allergy alert: Do not use if you have a history of allergy to local anesthetics such as procaine, butacaine, benzocaine or other "caine" anesthetics.

Sore throat warning: if sore throat is severe, persists for more than 2 days, is accompanied or followed by fever, headache, rash, swelling, nausea, or vomiting, consult a doctor promptly. If sore mouth symptoms do not improve in 7 days, or irritation, pain, or redness persists or worsens, see your dentist or doctor promptly.

Do not use

- if foil pouch has been previously opened
- for teething
- in children under 2 years of age

When using this product

- avoid contact with eyes

Keep out of reach of children.

If more than used for pain is accidently swallowed, get medical help or contact a Poison Control Center Immediately

Directions

- do not exceed recommended dosage

adults and children 2 years of age and older: use up to 4 times daily or as directed by a dentist or doctor

children under 12 years of age: should be supervised in the use of the product

children under 2 years of age: do not use

Other information

- store at 15-30 °C (59-86 °F)

Inactive ingredients

flavor, polyethylene goycol, sodium saccharin

Questions or comments?

1-800-238-4582

M-F: 8:00 a.m. - 4:30 p.m. ET

Principal Display Panel

HurriCaine One 2ct carton

Principal Display Panel

HurriCaine One 25ct carton